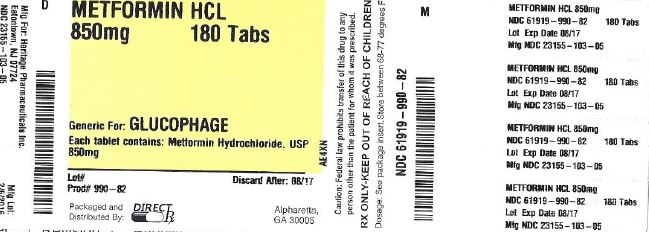 DRUG LABEL: METFORMIN HYDROCHLORIDE
NDC: 61919-990 | Form: TABLET
Manufacturer: Direct RX
Category: prescription | Type: HUMAN PRESCRIPTION DRUG LABEL
Date: 20160208

ACTIVE INGREDIENTS: METFORMIN HYDROCHLORIDE 850 mg/1 1
INACTIVE INGREDIENTS: POVIDONE K90; HYPROMELLOSE 2910 (6 MPA.S); MALTODEXTRIN; MAGNESIUM STEARATE; HYPROMELLOSE 2910 (5 MPA.S); POLYETHYLENE GLYCOL 400; BLACKBERRY; POVIDONE K30; STARCH, CORN

METFROMIN HCL

WARNINGS

Lactic acidosis is a rare, but serious, metabolic complication that can occur due to Metformin accumulation during treatment with Metformin Hydrochloride Tablets USP; when it occurs, it is fatal in approximately 50% of cases. Lactic acidosis may also occur in association with a number of pathophysiologic conditions, including diabetes mellitus, and whenever there is significant tissue hypoperfusion and hypoxemia. Lactic acidosis is characterized by elevated blood lactate levels (>5 mmol/L), decreased blood pH, electrolyte disturbances with an increased anion gap, and an increased lactate/pyruvate ratio. When Metformin is implicated as the cause of lactic acidosis, Metformin plasma levels >5 mcg/mL are generally found.
The reported incidence of lactic acidosis in patients receiving Metformin hydrochloride is very low (approximately 0.03 cases/1000 patient-years, with approximately 0.015 fatal cases/1000 patient-years). In more than 20,000 patient-years exposure to Metformin in clinical trials, there were no reports of lactic acidosis. Reported cases have occurred primarily in diabetic patients with significant renal insufficiency, including both intrinsic renal disease and renal hypoperfusion, often in the setting of multiple concomitant medical/surgical problems and multiple concomitant medications. Patients with congestive heart failure requiring pharmacologic management, in particular those with unstable or acute congestive heart failure who are at risk of hypoperfusion and hypoxemia, are at increased risk of lactic acidosis. The risk of lactic acidosis increases with the degree of renal dysfunction and the patient’s age. The risk of lactic acidosis may, therefore, be significantly decreased by regular monitoring of renal function in patients taking Metformin Hydrochloride Tablets USP and by use of the minimum effective dose of Metformin Hydrochloride Tablets USP. In particular, treatment of the elderly should be accompanied by careful monitoring of renal function. Metformin Hydrochloride Tablets USP treatment should not be initiated in patients ≥80 years of age unless measurement of creatinine clearance demonstrates that renal function is not reduced, as these patients are more susceptible to developing lactic acidosis. In addition, Metformin Hydrochloride Tablets USP should be promptly withheld in the presence of any condition associated with hypoxemia, dehydration, or sepsis. Because impaired hepatic function may significantly limit the ability to clear lactate, Metformin Hydrochloride Tablets USP should generally be avoided in patients with clinical or laboratory evidence of hepatic disease. Patients should be cautioned against excessive alcohol intake, either acute or chronic, when taking Metformin Hydrochloride Tablets USP, since alcohol potentiates the effects of Metformin hydrochloride on lactate metabolism. In addition, Metformin Hydrochloride Tablets USP should be temporarily discontinued prior to any intravascular radiocontrast study and for any surgical procedure (see also PRECAUTIONS).
The onset of lactic acidosis often is subtle, and accompanied only by nonspecific symptoms such as malaise, myalgias, respiratory distress, increasing somnolence, and nonspecific abdominal distress. There may be associated hypothermia, hypotension, and resistant bradyarrhythmias with more marked acidosis. The patient and the patient’s physician must be aware of the possible importance of such symptoms and the patient should be instructed to notify the physician immediately if they occur (see also PRECAUTIONS). Metformin Hydrochloride Tablets USP should be withdrawn until the situation is clarified. Serum electrolytes, ketones, blood glucose, and if indicated, blood pH, lactate levels, and even blood Metformin levels may be useful. Once a patient is stabilized on any dose level of Metformin Hydrochloride Tablets USP, gastrointestinal symptoms, which are common during initiation of therapy, are unlikely to be drug related. Later occurrence of gastrointestinal symptoms could be due to lactic acidosis or other serious disease.
Levels of fasting venous plasma lactate above the upper limit of normal but less than 5 mmol/L in patients taking Metformin Hydrochloride Tablets USP do not necessarily indicate impending lactic acidosis and may be explainable by other mechanisms, such as poorly controlled diabetes or obesity, vigorous physical activity, or technical problems in sample handling. (See also PRECAUTIONS.)
Lactic acidosis should be suspected in any diabetic patient with metabolic acidosis lacking evidence of ketoacidosis (ketonuria and ketonemia).
Lactic acidosis is a medical emergency that must be treated in a hospital setting. In a patient with lactic acidosis who is taking Metformin Hydrochloride Tablets USP, the drug should be discontinued immediately and general supportive measures promptly instituted. Because Metformin hydrochloride is dialyzable (with a clearance of up to 170 mL/min under good hemodynamic conditions), prompt hemodialysis is recommended to correct the acidosis and remove the accumulated Metformin. Such management often results in prompt reversal of symptoms and recovery. (See also CONTRAINDICATIONS and PRECAUTIONS.)